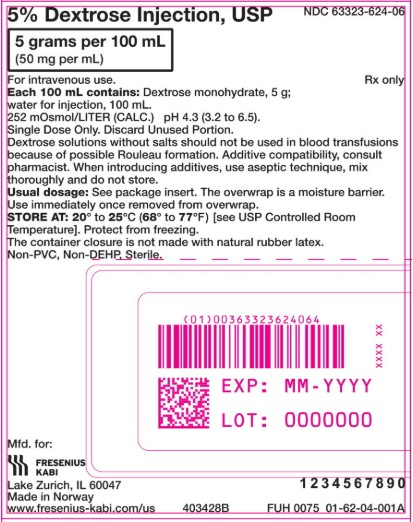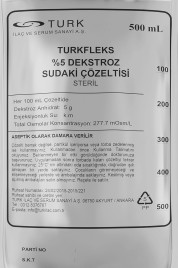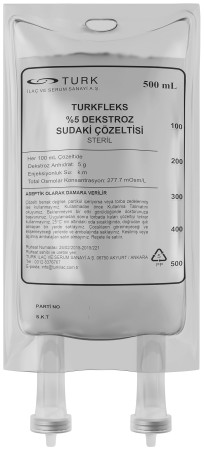 DRUG LABEL: Turkfleks 5% Dextrose Water Solution
NDC: 85160-300 | Form: INJECTION
Manufacturer: TURK ILAC VE SERUM SANAYI
Category: prescription | Type: HUMAN PRESCRIPTION DRUG LABEL
Date: 20250331

ACTIVE INGREDIENTS: ANHYDROUS DEXTROSE 5 g/100 mL

DESCRIPTION

NAME OF HUMAN MEDICAL PRODUCT TURKFLEKS %5 DEXTROSE solution in water Sterile 2. QUALITATIVE AND QUANTITATIVE COMPOSITION Active substance: Each 100 ml solution contains 5 g dextrose anhydrate. Osmolarity: approximately 277 mOsm/liter Calories: 200 kcal/liter Excipients: Water

PHARMACEUTICAL FORM Sterile solution for intravenous infusion. The solution is clear and free of particles.

CLINICAL FEATURES

Therapeutic indications - TURKFLEKS 5% DEXTROSE is indicated for the treatment of carbohydrate and fluid deficiency. - TURKFLEKS 5% DEXTROSE is also used as a diluent solution for drugs with which it is compatible in parenteral applications.

Dosage and method of administration Dosage / frequency and duration of administration: The dose to be administered should be determined by the physician for each patient based on the patient's age, body weight, clinical condition and laboratory studies. Serum glucose concentrations should be carefully monitored during treatment. Recommended doses for the treatment of carbohydrate and fluid deficiency: Adults, adolescents and the elderly 500 - 3000 ml per 24 hours.

Frequency and duration of application: The frequency and dose of application are adjusted by the physician according to the clinical condition of the patient. Method of application: Application is made intravenously with sterile apyrogen sets (peripheral or central veins). Rate of application: To prevent the development of hyperglycemia, the infusion rate should not exceed the patient's glucose oxidation capacity. Therefore, the highest dose that can be administered for adults should not exceed 5 mg per minute, and for infants and children, it should not exceed 10-18 mg/kg per minute depending on age and total body weight. When used as a diluent, the infusion rate is adjusted according to the recommended dose of the diluted drug. Additional information regarding special populations: Renal / Liver failure: Since there is no study specifically conducted for this population, there is no special dosage recommendation for this patient group.

Additional information regarding special populations: Renal/Liver failure: Since there is no study specifically conducted for this population, there is no specific dosage recommendation for this patient group. Pediatric population: The dose and infusion rate to be administered are adjusted by the physician according to the patient's weight, clinical and biological status, and concomitant therapy, as in adults. A dose of 20-100 ml/kg per 24 hours is generally recommended for this population, and this dose is adjusted according to body weight as follows: • 0-10 kg: 100 ml/kg/day • 10-20 kg: 1000 ml + 50 ml/day for each kilogram over 10 kg • > 20 kg: 1500 ml + 20 ml/day for each kilogram over 20 kg Geriatric population: Adult doses are also used in the elderly.

CONTRAINDICATIONS

Dekompanse diyabette, metabolik stres durumları gibi glukoz intoleransı durumlarında, hiperozmolar koma durumlarında, hiperglisemi durumlarında ve hiperlaktatemi durumunda kontrendikedir.

Dekstroz içeren çözeltiler mısır ya da mısır ürünlerine karşı aşırı duyarlılığı bulunan kişilerde kontrendike olabilir.

WARNINGS AND PRECAUTIONS

TURKFLEKS %5 DEKSTROZ izotonik bir çözeltidir. Yüksek hacimli infüzyonlar, su zehirlenmesi durumlarında veya oligüri/anüri ile seyreden ağır böbrek yetmezliği, kardiyak ve/veya pulmoner yetmezlik vakalarında dikkatli bir izlem altında uygulanmalıdır.
Dekstroz çözeltilerinin uygulanımı hiperglisemiye yol açabilir. Oluşabilecek bir hiperglisemi durumu iskemik beyin hasarını artırabileceği ve iyileşmeyi geciktirebileceğinden, akut iskemik inmelerden sonra TURKFLEKS %5 DEKSTROZ’un kullanılmaması önerilir.
Kafa travmasını takip eden ilk 24 saat içinde dekstroz infüzyonu uygulanmamalı ve intrakraniyal hipertansif dönemlerde kan glukoz düzeyi yakından izlenmelidir.
Tüm intravenöz infüzyonların başlangıcında dikkatli bir klinik izlem gerekir.
Uygulamalar düzenli olarak dikkatli bir gözlem altında yürütülmelidir. Klinik ve biyolojik parametreler, özellikle de kan glukoz düzeyleri izlenmelidir.
Hiperglisemi oluşursa infüzyon hızı ayarlanmalı veya insülin uygulanmalıdır. Gerektiğinde
parenteral potasyum ilavesi yapılmalıdır.
Dekstroz içeren çözeltiler diabetes mellitus olduğu bilinen ya da subklinik diyabetliler ile herhangi bir nedenle karbonhidrat intoleransı olan hastalara dikkatle uygulanmalıdır.

Böbrek yetmezliği olan hastalarda veya diabetes mellituslu hastalarda glukoz toleransı bozulabilir. Bu gibi hastalara TURKFLEKS %5 DEKSTROZ uygulandığında kan glukoz düzeyleri yakından izlenmeli ve gerekirse insülin ve/veya potasyum gereksinimleri yeniden belirlenerek tedavi buna uygun düzenlenmelidir.
Ozmotik diürez riskini azaltmak için yavaş infüzyon hızı kullanılmalıdır.
Elektrolitsiz dekstroz çözeltileri, kan transfüzyonu ile birlikte, infüzyon öncesinde veya sonrasında aynı infüzyon setinden uygulanmamalıdır, hemoliz ve eritrosit kümeleşmesine neden olabilirler.

Potasyum içermeyen çözeltilerin aşırı uygulaması durumu önemli bir hipokalemi durumuna yol açabilir. Serum potasyum düzeyleri normal düzeylerinde devam ettirilmeli ve gerekirse tedaviye potasyum eklenmelidir.
Çözeltiye eklenecek herhangi bir başka ilaçla olabilecek bir geçimsizlik riskini en aza indirmek için, karıştırma işleminden hemen sonra, uygulamadan önce ve uygulama sırasında belirli aralarla infüzyonu yapılacak son karışımda herhangi bir bulanıklık veya çökelme olup olmadığı kontrol edilmelidir.
Uygulama kontrollü bir infüzyon pompasıyla yapılacaksa, torbanın tümüyle boşalmadan önce pompanın çalışmasının durmuş olduğuna dikkat edilmelidir; aksi halde hava embolisi oluşabilir.
Çözelti, steril setler aracılığıyla intravenöz yoldan uygulanır. İntravenöz uygulamada kullanılan
setlerin 24 saatte bir değiştirilmesi önerilir.
Yalnızca çözelti berraksa, torba sağlam ve sızdırmıyorsa kullanılmalıdır.

OTHER SAFETY INFORMATION

Interactions with other medical products and other forms of interaction As with all parenteral solutions, compatibility with additional drugs should be evaluated by the physician before use. Drugs to be added should be evaluated in terms of compatibility before application according to the user manual provided with it. After adding drugs to TURKFLEKS 5% DEXTROSE, it should be ensured that there is no color change, insoluble particles and crystallization. Some drugs or solutions added to the solution may be incompatible. If other substances are to be added to the solution, aseptic technique should be used and shaken until mixed.

PREGNANCY

Genel tavsiye
Gebelik kategorisi: C
Çocuk doğurma potansiyeli bulunan kadınlar / Doğum kontrolü(Kontrasepsiyon)
Bilinen olumsuz bir etkisi bulunmamaktadır.

Gebelik dönemi
TURKFLEKS %5 DEKSTROZ’un gebe kadınlarda kullanımına ilişkin yeterli veri mevcut
değildir.
Hayvanlar üzerinde yapılan çalışmalar, gebelik /ve-veya/ embriyonal/fetal gelişim /ve- veya/doğum /ve-veya/ doğum sonrası gelişim üzerindeki etkiler bakımından yetersizdir (bkz. bölüm 5.3). İnsanlara yönelik potansiyel riskbilinmemektedir.
Doktor tarafından kesin gerekli görülmediği sürece (hastanın başka bir intravenöz sıvı ile
tedavi edilemediği durumlar dışında) gebelik döneminde kullanılmamalıdır.

LACTATION

Laktasyon dönemi
TURKFLEKS %5 DEKSTROZ çok gerekli olmadıkça emziren kadınlarda kullanılmamalıdır.

FEMALES AND MALES OF REPRODUCTIVE POTENTIAL

Üreme yeteneği / Fertilite
Üreme yeteneği/fertilite üzerine etkisi yoktur.

ADVERSE REACTIONS

Undesirable effects The undesirable effects observed during the use of 5% Dextrose in water solutions are as follows: Very common (≥1/10); common (≥1/100 to <1/10); uncommon (≥1/1,000 to <1/100); rare (≥1/10,000 to <1/1,000); very rare (<1/10,000), not known (cannot be based on available data). Metabolism and nutritional disorders Not known: Fluid and electrolyte imbalances*; hyperglycemia and dehydration** Renal and urinary disorders Not known: Polyuria Surgical and medical procedures*** Not known: Injection site infection; local pain or reaction; vein irritation; development of venous thrombosis and phlebitis spreading from the injection site; extravasation; hypervolemia.

* Hypokalemia, hypomagnesemia and hypophosphatemia etc. ** Adverse reactions generally seen as a result of incorrect parenteral administration *** Adverse reactions that can be seen depending on the application technique Adverse reactions related to drugs added to the solution can also be seen; the nature of these undesirable effects is determined by the properties of the added drug. Infusion should be terminated if an undesirable effect is observed. Reporting of suspected adverse reactions Reporting of suspected adverse reactions to drugs after licensing is of great importance. Reporting allows continuous monitoring of the benefit/risk balance of the drug. Healthcare professionals should report any suspected adverse reactions to the Turkish Pharmacovigilance Center (TÜFAM) (www.titck.gov.tr; e-mail: tufam@titck.gov.tr; tel: 0 800 314 00 08; fax: 0 312 218 35 99).

OVERDOSAGE

Overdose and treatment Rapid or prolonged administration of TURKFLEKS %5 DEXTROSE may lead to hyperosmolarity, dehydration, hyperglycemia, hyperglucosuria and osmotic diuresis (due to hyperglycemia). Patients may develop edema and water intoxication (with hyponatremia) due to fluid overload. If the overdose is due to drugs added to the solution, the signs and symptoms of overdose depend on the properties of the added drug. If the dose is accidentally exceeded during treatment, the administration should be discontinued and the patient should be monitored for signs and symptoms related to the drug applied. Symptomatic and supportive treatments should be applied when necessary.

PHARMACOKINETICS

Emilim:
TURKFLEKS %5 DEKSTROZ intravenöz uygulama için geliştirilmiş bir ürün olduğundan bu bölümle ilgili bir bilgi bulunmamaktadır.
Dağılım:
Glukoz saatte 0.5 g/kg’a kadar olan dozlarda glukozüriye yol açmaksızın uygulanabilir. En yüksek infüzyon hızı olan saatte 0.8 g/kg hızında, uygulanan glukozun yaklaşık %95’i vücutta kalır.
Biyotransformasyon:
Glukoz vücutta kolaylıkla pirüvik asit veya laktik asit yolu ile tamamen metabolize olarak
enerji sağlar ve büyük oranda karbondioksit ile suya dönüşür.
Eliminasyon:
Biyotransformasyon sonucu oluşan karbondioksit akciğerlerle, su ise esas olarak böbrekler yoluyla az miktarda ise ter, feçes ve soluk vermeyle atılır.

PHARMACODYNAMICS

PHARMACOLOGICAL PROPERTIES 5.1. Pharmacodynamic properties. Pharmacotherapeutic group: Parenteral nutrition solutions / Carbohydrates ATC code: B05BA03. TURKFLEKS %5 DEXTROSE contains 5 grams of dextrose (D-glucose) anhydrate (C6H12O6) in every 100 ml solution. Dextrose anhydrate has a molecular weight of approximately 180.2. 1 gram provides energy equivalent to glucose, i.e. 4 calories. TURKFLEKS %5 DEXTROSE provides 200 kcal calories per liter. Moreover, a non-ionic hydration is provided by glucose infusion. Dextrose solutions are also given as a carbohydrate source in parenteral nutrition. However, more concentrated forms are preferred for this. The pharmacodynamic properties of TURKFLEKS 5% DEXTROSE consist of the properties of glucose, which is the active ingredient and the main energy source in cellular metabolism. TURKFLEKS 5% DEXTROSE is an almost isotonic solution with an osmolarity of approximately 277 mOsm/l. TURKFLEKS 5% DEXTROSE is used in the clinic to provide electrolyte-free hydration and may stimulate diuresis depending on the clinical condition of the patient. The pharmacodynamic properties of the drugs added to the solution are the same as the pharmacodynamic properties of the added drug.

OTHER SAFETY INFORMATION

Incompatibilities As with all parenteral solutions, before adding a drug to TURKFLEKS %5 DEXTROSE, it should be evaluated whether these drugs are compatible with the solution. It is the responsibility of the physician performing the application to decide whether the added drug is compatible by checking whether there is a color change and/or precipitation, insoluble compounds or crystallization after the drug is added. The compatibility of the drug to be added to TURKFLEKS %5 DEXTROSE should be decided by using the product information of the drug to be added. Before adding a drug to the solution, it should be confirmed that TURKFLEKS %5 DEXTROSE is soluble and stable at its pH. TURKFLEKS %5 DEXTROSE should be used immediately after a compatible drug is added to it. Drugs known to be incompatible should not be added.

Shelf life 36 months In-use shelf life: From a microbiological point of view, it should be used immediately after preparation for use. In cases where it is not used immediately, the determination of the storage conditions and duration is the responsibility of the person adding/diluting the drug and the duration is normally not longer than 24 hours at 2-8 °C unless this process is carried out under validated aseptic conditions.

Special precautions for storage No special storage requirements. Stored at room temperature below 25 °C, away from direct light.

DISPOSAL AND WASTE HANDLING

Disposal of residues of medicinal products for human use and other special precautions Unused products or waste materials should be disposed of in accordance with the 'Regulation on Control of Medical Waste' and 'Regulation on Control of Packaging Waste'.
For single use only.
Other special precautions related to the application:
The solutions to be infused should be visually inspected before use; only clear, particle-free and intact products should be used. After the application kit is attached to the product, the application should be started as soon as possible.
To prevent an air embolism due to residual air in the bag, serial connection with other infusion fluids should be avoided.
The solution should be administered using aseptic technique through a sterile administration set. Liquid should be passed through the administration set before use to prevent air from entering the system.
Additional drugs may be added before and during infusion under aseptic conditions. The isotonicity of the final product must be determined before parenteral administration.
The added drug must be completely mixed with the solution before administration to the patient. Solutions containing additional drugs should be used immediately after the addition of the drug; they should not be stored for later use.
Addition of additional drug to the solution or incorrect administration technique may cause fever reaction due to pyrogen contamination. In case of adverse reaction, the infusion should be discontinued immediately.

Translated with DeepL.com (free version)

INSTRUCTIONS FOR USE

1. Check that the outer packaging is intact and free from leaks; do not use if the packaging is damaged.
2. Tear open the protective outer packaging.
3. Check that the bag in the protective packaging is intact by squeezing it.
4. Check that the solution in the bag is clear and free of foreign matter.
Please check.
Preparations for application:
1. Hang the bag.
2. Remove the protective cap from the application tip.
3. Insert the spoon of the administration set firmly into the administration tip. Administer the solution to the patient
The instructions for use of the kit must be followed for its application.
Adding additional medication:
Caution: As with all parenteral solutions, all substances to be added to the product must be compatible with the product. If the product is to be added, compatibility should be checked in the final mixture before administration to the patient.

Translated with DeepL.com (free version)

- Adding medication before application:
1. The drug administration tip of the bag is disinfected.
2. The drug to be added is administered with a syringe with a 19-22 gauge needle.
3. The solution and the added drug are thoroughly mixed. For concentrated medication such as potassium chloride, the application outlet of the bag is tapped gently in the up position to ensure that the medication is fully mixed with the solution.
Caution: Bags with additional medication should not be stored.
- Adding medication during administration:
1. Clamp the set closed.
2. The drug application tip is disinfected.
3. The drug to be added is administered with a syringe with a 19-22 gauge needle.
4. Remove the bag from the strap and turn it upside down.
5. In this position, gently tap the administration outlet and injection inlet of the bag.
The solution and the additional drug are mixed by tapping.
6. Return the bag to its original position, open the clamp and continue the application.

Translated with DeepL.com (free version)

HEALTH CARE PROVIDER LETTER

March 31, 2025

Subject: Temporary importation of Turkfleks %5 Dextrose Solution from Turk Ilac located in Ankara-TURKEY to address drug shortages per:

https://dps.fda.gov/drugshortages/activeingredient/dextrose-monohydrate-5--injection

To prevent a shortage of large volume parenteral fluid drug products, Turk Ilac ve Serum Sanayi is coordinating with the U.S. Food and Drug Administration (FDA) to temporarily import Turkfleks %5 Dextrose Solution 100ml, 150ml, 250ml, 500ml, 1000ml from Turk Ilac ve Serum Sanayi manufacturing facility located in Ankara/TURKEY. FDA has not approved these products manufactured by Turk Ilac ve Serum Sanayi.

Effective immediately, and during this temporary period, Turk Ilac ve Serum Sanayi will offer the following imported product from Turk Ilac ve Serum Sanayi facility located in Ankara/TURKEY:

Product Name and Description | Volume | Bags per Box | NDC Code
Turkfleks %5 Dextrose Solution | 100ml | 100 | 85160-300-10
Turkfleks %5 Dextrose Solution | 150ml | 100 | 85160-300-20
Turkfleks %5 Dextrose Solution | 250ml | 100 | 85160-300-30
Turkfleks %5 Dextrose Solution | 500ml | 100 | 85160-300-40
Turkfleks %5 Dextrose Solution | 1000ml | 50 | 85160-300-50

Please note the following:

- Upon receiving Submission Acceptance Turk Ilac ve Serum Sanayi will have bag labels written in both Turkish and English.
- The bag labels will contain the active pharmaceutical ingredient, concentration, volume, and NDC code in English.
- The imported products' administration port system is fully compatible with sets marketed in the United States.
- The imported products use a carton box that is taped closed. To avoid damage to the solution container, take care not to use sharp instruments to open the box.
- The imported products do not contain barcodes on the unit label. Alternative procedures should be followed to ensure that the correct drug product is being used in all systems and processes and administered to individual patients. For example, institutions should consider manually inputting the product into their systems and confirm that barcode systems do not provide incorrect information when the product is scanned.
- %5 Dextrose Solution is available only by prescription in the United States. However, the imported products do not have the statement "Rx only" on the labeling.
- USE A NEW BAG IF PARTICULATES ARE VISIBLE OR IF THE IV BAG CONTAINS A LEAK.

Additional key differences in the labeling between the FDA-approved product and the imported products are stated in the product comparison table at the end of this letter as follows:

Table 1. Key differences between FDA-approved and Turkfleks %5 Dextrose Solution

Table 2. Label images of FDA-approved and Turkfleks %5 Dextrose Solution

Reporting Adverse Events or Product Quality Issues

To report adverse events associated with these imported products, please use the contact us at info@turkilac.com.tr.

Adverse events or quality problems experienced with the use of these imported products may also be reported to the FDA's MedWatch Adverse Event Reporting program either online, by regular mail or by fax:

- Complete and submit the report Online: www.fda.gov/medwatch/report.htm
- Regular mail or Fax: Download form www.fda.gov/MedWatch/getforms.htm

or call 1-800332-1088 to request a reporting form, then complete and return to the address on the preaddressed form or submit by fax to 1-800-FDA-0178 (1-800-332-0178).

Sincerely,

Mehmet Berat Battal

Table 1: Key Differences between FDA Approved product and Turkfleks %5 Dextrose Solution

 | FDA- Approved Product | Turkfleks Import from Turkey
Product Name | 5% Dextrose Injection USP, 500 mL | Turkfleks 5% Dextrose Water Solution
Language of the Labels | English | Turkish*
Indications | These intravenous solutions are indicated for use in adults and pediatric patients as sources of calories and water for hydration. | - TURKFLEKS 5% DEXTROSE is indicated for the treatment of carbohydrate and fluid deficiency.; - TURKFLEKS 5% DEXTROSE is also used as a diluent solution for drugs that are compatible with it in parenteral applications.
Active Ingredients | Each 100 mL of 5% Dextrose Injection, USP, contains dextrose monohydrate, 5 g in water for injection. The caloric value is 170 kcal/L. The osmolarity is 252 mOsmol/L (calc.), which is slightly hypotonic. The solution pH is 4.3 (3.2 to 6.5). | Each 100 mL of 5% Dextrose Injection contains:; anyhdrat Dextrose 5 g; Water for Injection qs; pH: 4.4 (3.5–6.5); Calculated Osmolarity: 277 mOsmol/liter; Calories per liter: 200 kcal
Store Conditions | Store at room temperature 25C/77F | Store at below 30C
Container Type | freeflex® bags | Polypropylene

*Upon receiving Submission Acceptance Turk Ilac ve Serum Sanayi will have bag labels written in both Turkish and English.

Table 2: Label Images of FDA-approved and Turkfleks %5 Dextrose Solution

FDA-approved Product

Turkfleks %0.9 Sodium Chloride Injection